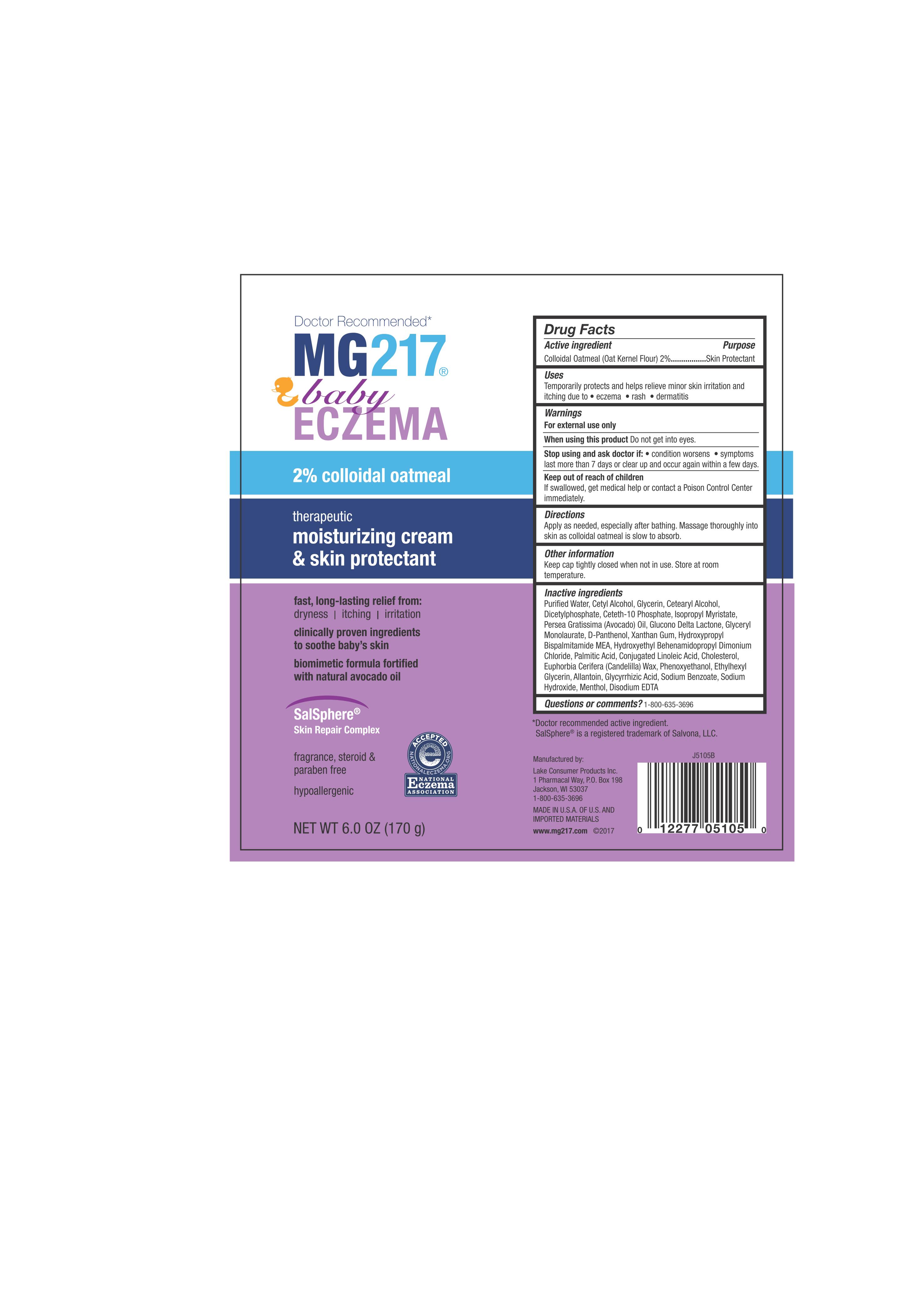 DRUG LABEL: MG217 Baby Eczema
NDC: 68093-5105 | Form: LOTION
Manufacturer: Wisconsin Pharmacal Company
Category: otc | Type: HUMAN OTC DRUG LABEL
Date: 20171128

ACTIVE INGREDIENTS: OATMEAL 0.02 g/1 g
INACTIVE INGREDIENTS: CETYL ALCOHOL; ETHYLHEXYLGLYCERIN; ALLANTOIN; GLYCYRRHIZIN; GLYCERYL 1-LAURATE; HYDROXYETHYL BEHENAMIDOPROPYL DIMONIUM CHLORIDE; SODIUM HYDROXIDE; HYDROXYPROPYL BISPALMITAMIDE MONOETHANOLAMIDE; DEXPANTHENOL; GLUCONOLACTONE; CETOSTEARYL ALCOHOL; DIHEXADECYL PHOSPHATE; CANDELILLA WAX; CETETH-10 PHOSPHATE; EDETATE DISODIUM; WATER; MENTHOL, (+)-; ISOPROPYL MYRISTATE; AVOCADO OIL; SODIUM BENZOATE; GLYCERIN; XANTHAN GUM; PALMITIC ACID; CONJUGATED LINOLEIC ACID; CHOLESTEROL; PHENOXYETHANOL

Active Ingredient

Colloidal Oatmeal (Oat Kernel Flour) 2%

Purpose

Skin Protectant

Uses

Temporarily protects and helps relieve minor skin irritation and itching due to

- eczema
- rash
- dermatitis

WARNINGS

For external use only

When using this product Do not get into eyes

Stop using and ask doctor if:

- condition worsens
- symptoms last more than 7 days or clear up and occur again wtihin a few days

Keep out of reach of children

If swallowed, get medical help or contact a Poison Control Center immediately

Directions

Apply as needed, especially after bathing. Massage thoroughly into skin as colloidal oatmeal is slow to absorb.

Other Information

Keep cap tightly closed when not in use. Store at room temperature.

Inactive ingredients

Puriﬁed Water, Cetyl Alcohol, Glycerin, Cetearyl Alcohol, Dicetylphosphate, Ceteth-10 Phosphate, Isopropyl Myristate, Persea Gratissima (Avocado) Oil, Glucono Delta Lactone, Glyceryl Monolaurate, D-Panthenol, Xanthan Gum, Hydroxypropyl Bispalmitamide MEA, Hydroxyethyl Behenamidopropyl Dimonium Chloride, Palmitic Acid, Conjugated Linoleic Acid, Cholesterol, Euphorbia Cerifera (Candelilla) Wax, Phenoxyethanol, Ethylhexyl Glycerin, Allantoin, Glycyrrhizic Acid, Sodium Benzoate, Sodium Hydroxide, Menthol, Disodium EDTA

Questions or comments?

1-800-635-3696